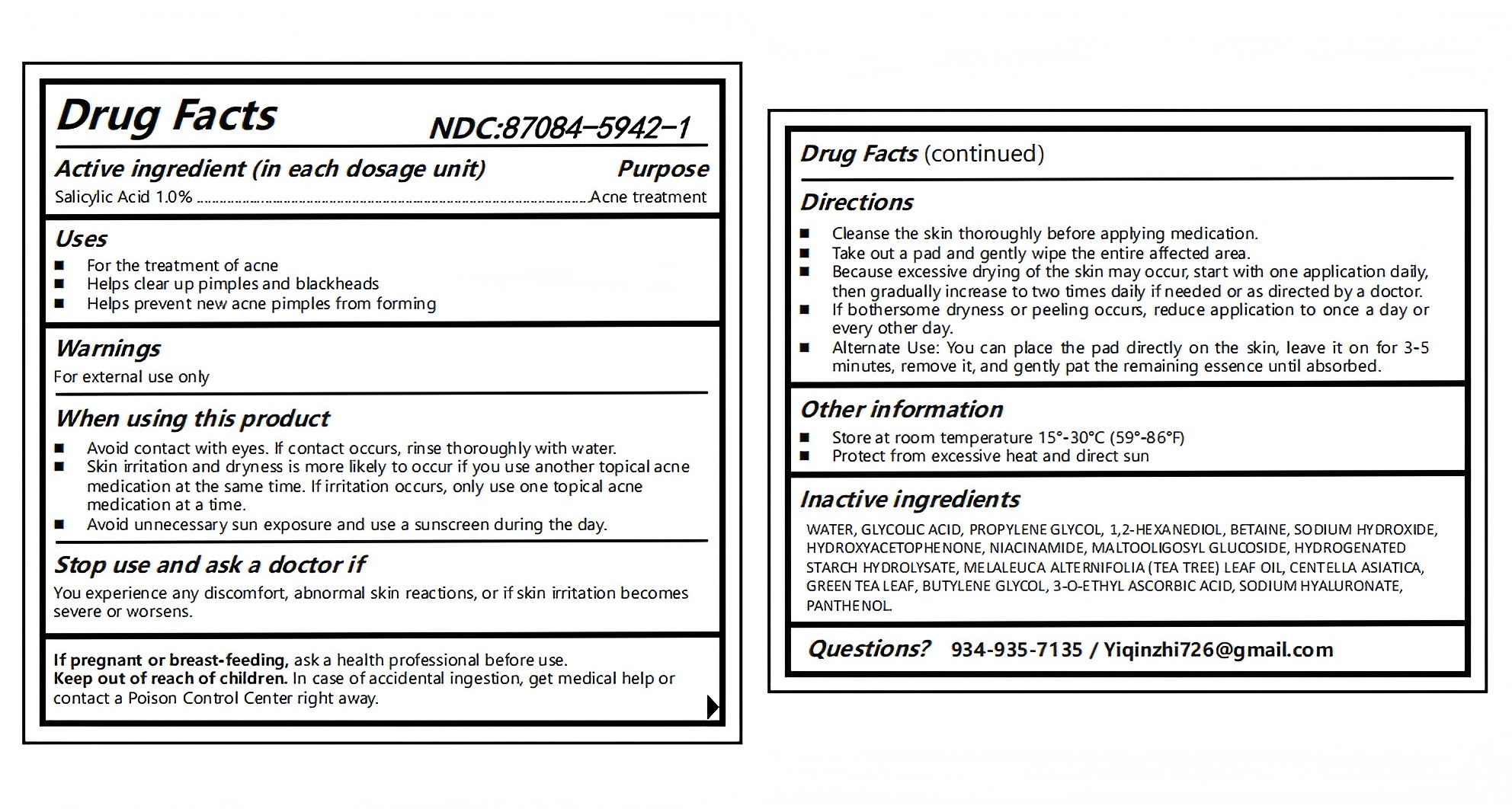 DRUG LABEL: JTOPYRT
NDC: 87084-5942 | Form: SWAB
Manufacturer: Guangzhou Yixiang Trading Co., Ltd.
Category: otc | Type: HUMAN OTC DRUG LABEL
Date: 20250904

ACTIVE INGREDIENTS: SALICYLIC ACID 1 g/100 g
INACTIVE INGREDIENTS: MALTOOLIGOSYL GLUCOSIDE 0.235 g/100 g; BETAINE 0.5 g/100 g; BUTYLENE GLYCOL 0.12 g/100 g; GREEN TEA LEAF 0.12 g/100 g; MELALEUCA ALTERNIFOLIA (TEA TREE) LEAF OIL 0.135 g/100 g; PROPYLENE GLYCOL 1 g/100 g; WATER 91.025 g/100 g; HYDROGENATED STARCH HYDROLYSATE 0.135 g/100 g; GLYCOLIC ACID 2 g/100 g; 1,2-HEXANEDIOL 0.75 g/100 g; NIACINAMIDE 0.4 g/100 g; SODIUM HYDROXIDE 0.46 g/100 g; CENTELLA ASIATICA 0.12 g/100 g; SODIUM HYALURONATE 0.1 g/100 g; HYDROXYACETOPHENONE 0.35 g/100 g; 3-O-ETHYL ASCORBIC ACID 0.75 g/100 g; PANTHENOL 0.8 g/100 g

Active ingredient(s)

Salicylic Acid 1.0%

Purpose(s)

Acne treatment

Uses

- For the treatment of acne
- Helps clear up pimples and blackheads
- Helps prevent new acne pimples from forming

Warnings

For external use only

When using this product

- Avoid contact with eyes. If contact occurs, rinse thoroughly with water.
- Skin irritation and dryness is more likely to occur if you use another topical acne

medication at the same time. If irritation occurs, only use one topical acne
medication at a time.

- Avoid unnecessary sun exposure and use a sunscreen during the day.

Stop use and ask a doctor if

You experience any discomfort, abnormal skin reactions, or if skin irritation becomes
severe or worsens.

Pregnancy or breast feeding section

If pregnant or breast-feeding, ask a health professional before use.

Keep out of reach of children

In case of accidental ingestion, get medical help or contact a Poison Control Center right away.

Directions

- Cleanse the skin thoroughly before applying medication.
- Take out a pad and gently wipe the entire affected area.
- Because excessive drying of the skin may occur, start with one application daily, then gradually increase to two times daily if needed or as directed by a doctor.
- If bothersome dryness or peeling occurs, reduce application to once a day or every other day.
- Alternate Use: You can place the pad directly on the skin, leave it on for 3-5 minutes, remove it, and gently pat the remaining essence until absorbed

Other information

- Store at room temperature 15°-30°C (59°-86°F)
- Protect from excessive heat and direct sun

Inactive ingredients

WATER, GLYCOLIC ACID, PROPYLENE GLYCOL, 1,2-HEXANEDIOL, BETAINE, SODIUM HYDROXIDE, HYDROXYACETOPHENONE, NIACINAMIDE, MALTOOLIGOSYL GLUCOSIDE, HYDROGENATED STARCH HYDROLYSATE, MELALEUCA ALTERNIFOLIA (TEA TREE) LEAF OIL, CENTELLA ASIATICA, GREEN TEA LEAF, BUTYLENE GLYCOL, 3-O-ETHYL ASCORBIC ACID, SODIUM HYALURONATE, PANTHENOL.

Questions or comments?

934-935-7135 / Yiqinzhi726@gmail.com

Box Front Pane

Professional and scientific skin care Pore
Deeply cleanse the skin, remove excess oil, purify pores, and refine the skin texture.
60 PADS Double Sided